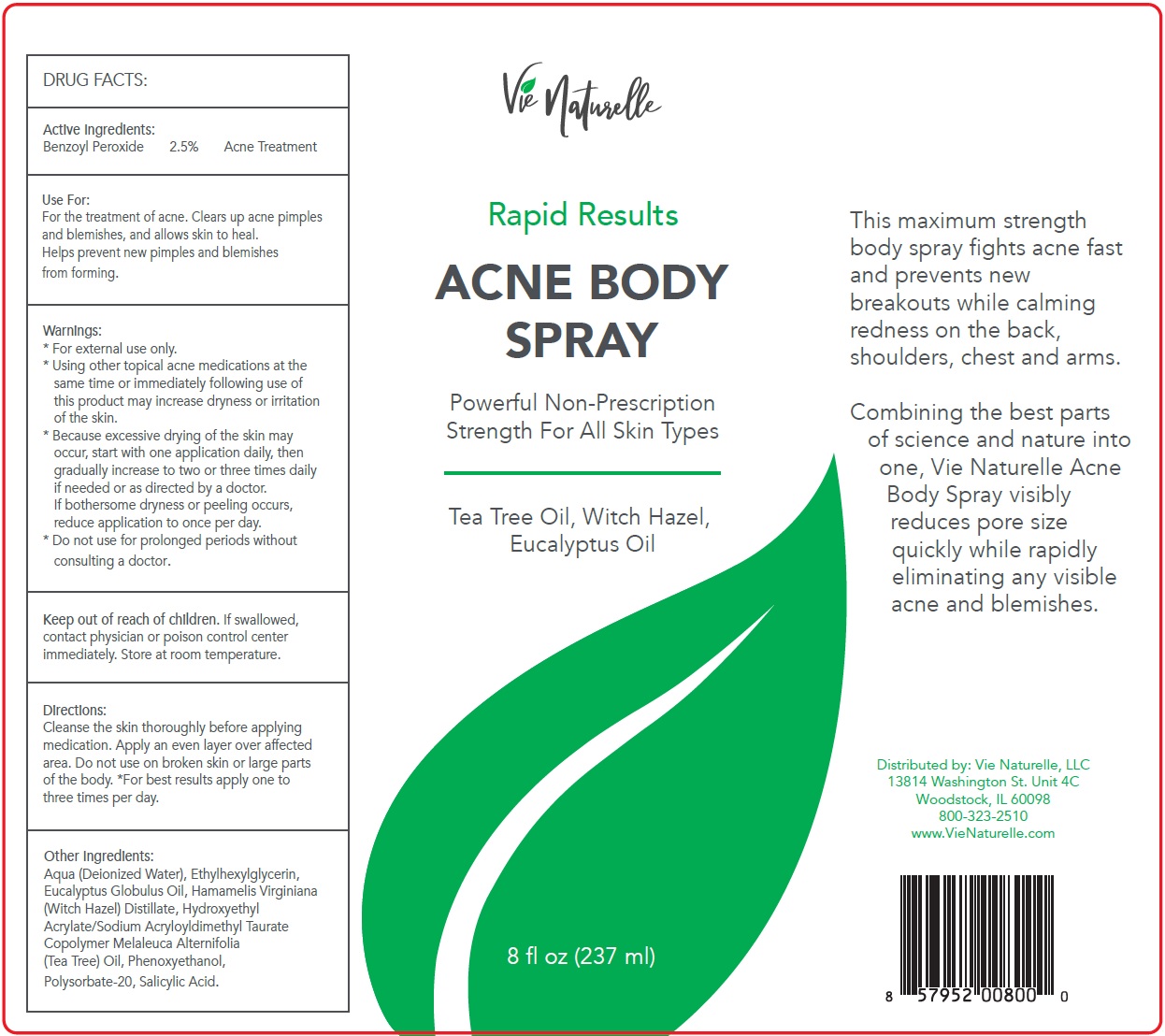 DRUG LABEL: VIE NATURELLE ACNE BODY
NDC: 73350-105 | Form: LIQUID
Manufacturer: TNT PRO SERIES
Category: otc | Type: HUMAN OTC DRUG LABEL
Date: 20231105

ACTIVE INGREDIENTS: BENZOYL PEROXIDE 25 mg/1 mL
INACTIVE INGREDIENTS: WATER; ETHYLHEXYLGLYCERIN; EUCALYPTUS OIL; WITCH HAZEL; MELALEUCA ALTERNIFOLIA LEAF; PHENOXYETHANOL; POLYSORBATE 20; SALICYLIC ACID

VIE NATURELLE ACNE BODY SPRAY

Active Ingredients:

Benzoyl Peroxide 2.5%

PURPOSE

Acne Treatment

Use For:

For the treatment of acne. Clears up acne pimples and blemishes, and allows skin to heal. Helps prevent new pimples and blemishes from forming.

Warnings:

- For external use only.
- Using other topical acne medications at the same time or immediately following use of this product may increase dryness or irritation of the skin.
- Because excessive drying of the skin may occur, start with one application daily, then gradually increase to two or three times daily if needed or as directed by a doctor. If bothersome dryness or peeling occurs, reduce application to once per day.

Do not use

for prolonged periods without consulting a doctor.

Keep out of reach of children.

If swallowed, contact physician or poison control center immediately. Store at room temperature.

Directions:

Cleanse the skin thoroughly before applying medication. Apply an even layer over affected area. Do not use on broken skin or large parts of the body. *For best results apply one to three times per day.

Other Ingredients:

Aqua (Deionized Water), Ethylhexylglycerin, Eucalyptus Globulus Oil, Hamamelis Virginiana (Witch Hazel) Distillate, Hydroxyethyl Acrylate/Sodium Acryloyldimethyl Taurate Copolymer Melaleuca Alternifolia (Tea Tree) Oil, Phenoxyethanol, Polysorbate-20, Salicylic Acid.